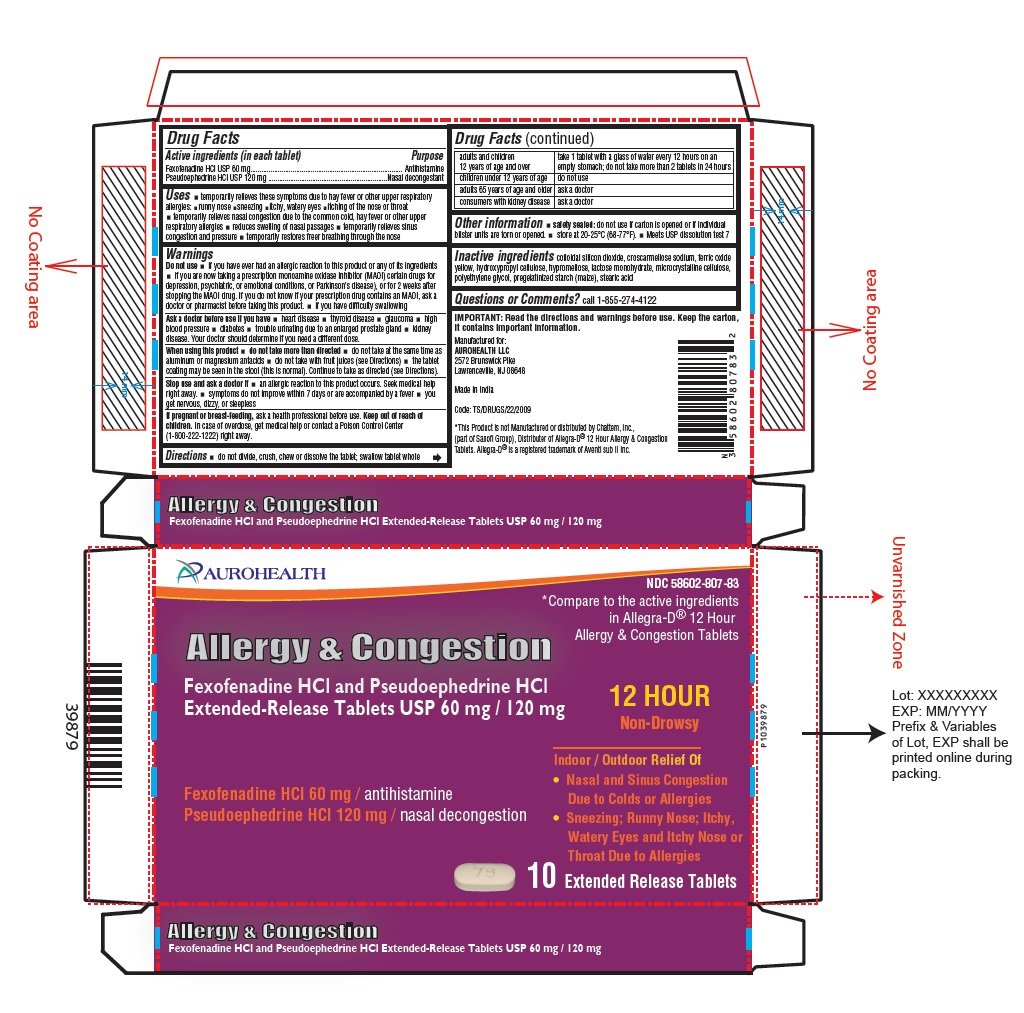 DRUG LABEL: Fexofenadine Hydrochloride and Pseudoephedrine Hydrochloride
NDC: 58602-807 | Form: TABLET, FILM COATED, EXTENDED RELEASE
Manufacturer: Aurohealth LLC
Category: otc | Type: Human OTC Drug Label
Date: 20240626

ACTIVE INGREDIENTS: FEXOFENADINE HYDROCHLORIDE 60 mg/1 1; PSEUDOEPHEDRINE HYDROCHLORIDE 120 mg/1 1
INACTIVE INGREDIENTS: SILICON DIOXIDE; CROSCARMELLOSE SODIUM; FERRIC OXIDE YELLOW; HYPROMELLOSE 2208 (100000 MPA.S); MICROCRYSTALLINE CELLULOSE; LACTOSE MONOHYDRATE; HYDROXYPROPYL CELLULOSE (110000 WAMW); POLYETHYLENE GLYCOL 6000; POLYETHYLENE GLYCOL 400; STARCH, CORN; STEARIC ACID

Fexofenadine Hydrochloride and Pseudoephedrine Hydrochloride Extended-Release Tablets USP

Drug Facts

Active ingredients (in each tablet)
Fexofenadine HCl USP 60 mg
Pseudoephedrine HCl USP 120 mg

Purpose

Antihistamine
Nasal decongestant

Uses

- temporarily relieves these symptoms due to hay fever or other upper respiratory allergies:
- runny nose
- sneezing
- itchy, watery eyes
- itching of the nose or throat
- temporarily relieves nasal congestion due to the common cold, hay fever or other upper respiratory allergies
- reduces swelling of nasal passages
- temporarily relieves sinus congestion and pressure
- temporarily restores freer breathing through the nose

Warnings

Do not use

- if you have ever had an allergic reaction to this product or any of its ingredients
- if you are now taking a prescription monoamine oxidase inhibitor (MAOI) certain drugs for depression, psychiatric, or emotional conditions, or Parkinson’s disease), or for 2 weeks after stopping the MAOI drug. If you do not know if your prescription drug contains an MAOI, ask a doctor or pharmacist before taking this product.
- if you have difficulty swallowing

Ask a doctor before use if you have

- heart disease
- thyroid disease
- glaucoma
- high blood pressure
- diabetes
- trouble urinating due to an enlarged prostate gland
- kidney disease. Your doctor should determine if you need a different dose.

When using this product

- do not take more than directed
- do not take at the same time as aluminum or magnesium antacids
- do not take with fruit juices (see Directions)
- the tablet coating may be seen in the stool (this is normal). Continue to take as directed (see Directions).

Stop use and ask a doctor if

- an allergic reaction to this product occurs. Seek medical help right away.
- symptoms do not improve within 7 days or are accompanied by a fever
- you get nervous, dizzy, or sleepless

If pregnant or breast-feeding, ask a health professional before use.

Keep out of reach of children.

In case of overdose, get medical help or contact a Poison Control Center (1-800-222-1222) right away.

Directions

- do not divide, crush, chew or dissolve the tablet; swallow tablet whole

adults and children 12 years of age and over | take 1 tablet with a glass of water every 12 hours on an empty stomach; do not take more than 2 tablets in 24 hours
children under 12 years of age | do not use
adults 65 years of age and older | ask a doctor
consumers with kidney disease | ask a doctor

Other information

- safety sealed: do not use if carton is opened or if individual blister units are torn or opened.
- store at 20-25°C (68-77°F).
- Meets USP dissolution test 7

Inactive ingredients

colloidal silicon dioxide, croscarmellose sodium, ferric oxide yellow, hydroxypropyl cellulose, hypromellose, lactose monohydrate, microcrystalline cellulose, polyethylene glycol, pregelatinized starch (maize), stearic acid
Questions or Comments?
call 1-855-274-4122
IMPORTANT: Read the directions and warnings before use. Keep the carton, it contains important information.
Manufactured for:
AUROHEALTH LLC
2572 Brunswick Pike
Lawrenceville, NJ 08648
Made in India
Code: TS/DRUGS/22/2009

PACKAGE LABEL-PRINCIPAL DISPLAY PANEL - 1 x 10 Blister Carton

AUROHEALTH
NDC 58602-807-83
*Compare to the active ingredients
in Allegra-D® 12 Hour
Allergy & Congestion Tablets
Allergy & Congestion
Fexofenadine HCl and Pseudoephedrine HCl
Extended-Release Tablets USP 60 mg / 120 mg
Fexofenadine HCl 60 mg / antihistamine
Pseudoephedrine HCl 120 mg / nasal decongestion
12 HOUR
Non-Drowsy
Indoor / Outdoor Relief Of

- Nasal and Sinus Congestion Due to Colds or Allergies
- Sneezing; Runny Nose; Itchy, Watery Eyes and Itchy Nose or Throat Due to Allergies

10 Extended Release Tablets